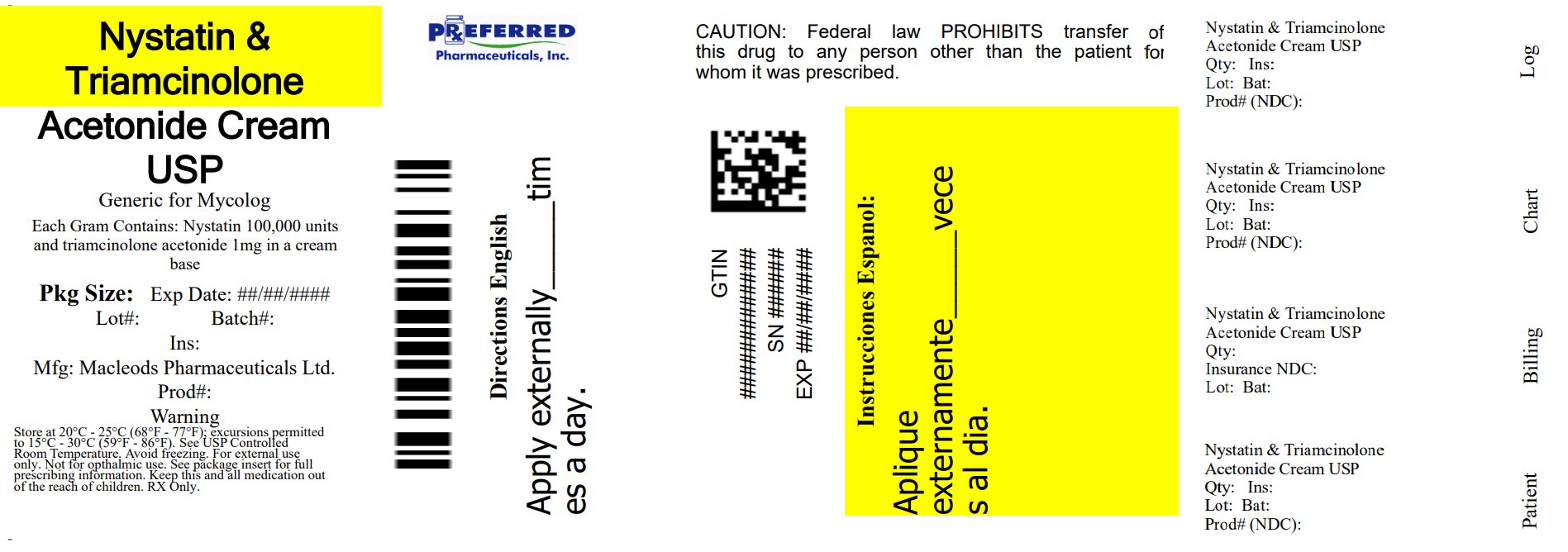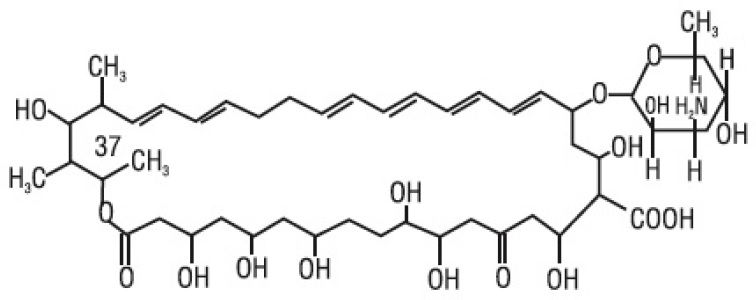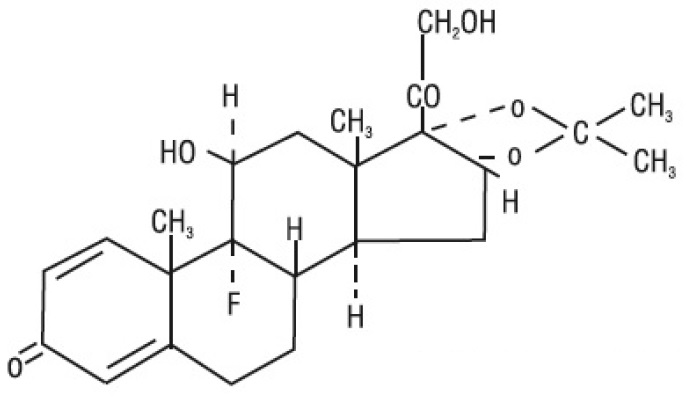 DRUG LABEL: Nystatin and triamcinolone acetonide
NDC: 68788-8662 | Form: CREAM
Manufacturer: Preferred Pharmaceuticals Inc.
Category: prescription | Type: HUMAN PRESCRIPTION DRUG LABEL
Date: 20260116

ACTIVE INGREDIENTS: NYSTATIN 100000 [USP'U]/1 g; TRIAMCINOLONE ACETONIDE 1 mg/1 g
INACTIVE INGREDIENTS: PETROLATUM; TITANIUM DIOXIDE; POLYSORBATE 60; CETEARETH-15; GLYCERYL MONOSTEARATE; PROPYLPARABEN; METHYLPARABEN; PROPYLENE GLYCOL; POLYETHYLENE GLYCOL 400; SORBITOL; SORBIC ACID; WATER; DIMETHICONE, UNSPECIFIED; ALUMINUM HYDROXIDE; SILICON DIOXIDE

Nystatin and Triamcinolone Acetonide Cream, USP
Rx only
FOR EXTERNAL USE ONLY • NOT FOR OPHTHALMIC USE

DESCRIPTION

Nystatin and triamcinolone acetonide cream, USP for dermatologic use contain the antifungal agent nystatin and the synthetic corticosteroid triamcinolone acetonide.
Nystatin, USP is a polyene antimycotic obtained from Streptomyces noursei. It is a yellow to light tan powder, Freely soluble in dimethylformamide and in dimethyl sulfoxide; very slightly soluble in methanol; practically insoluble or insoluble in water, in alcohol, in n-propyl alcohol, in n-butyl alcohol, in chloroform and in ether.
Structural formula:

C47H75NO17 MW= 926.13
Triamcinolone acetonide, USP is designated chemically as 9-fluoro-11β, 16α, 17, 21- tetrahydroxypregna-1, 4-diene-3, 20-dione cyclic 16, 17-acetal with acetone. The white to cream crystalline powder has a slight odor, Sparingly soluble in dehydrated alcohol, in chloroform and in methanol, Practically insoluble in water.
Structural formula:

C24H31FO6 MW= 434.50
Nystatin and triamcinolone acetonide cream, USP is a soft, smooth, light yellow to buff colored cream. Each gram provides 100,000 USP Nystatin units and 1 mg Triamcinolone Acetonide USP in a cream base with aluminium hydroxide, ceteareth 15, glyceryl monostearate, methyl paraben, non-crystallizing sorbitol solution, polysorbate 60, polyethylene glycol 400 monostearate, propylene glycol, propyl paraben, simethicone emulsion, sorbic acid, titanium dioxide white petrolatum, purified water.

CLINICAL PHARMACOLOGY

Nystatin
Nystatin exerts its antifungal activity against a variety of pathogenic and nonpathogenic yeasts and fungi by binding to sterols in the cell membrane. The binding process renders the cell membrane incapable of functioning as a selective barrier. Nystatin provides specific anticandidal activity to Candida (Monilia) albicans and other Candida species, but is not active against bacteria, protozoa, trichomonads, or viruses.

Nystatin is not absorbed from intact skin or mucous membranes.
Triamcinolone Acetonide
Triamcinolone acetonide is primarily effective because of its anti-inflammatory, antipruritic and vasoconstrictive actions, characteristic of the topical corticosteroid class of drugs. The pharmacologic effects of the topical corticosteroids are well known; however, the mechanisms of their dermatologic actions are unclear. Various laboratory methods, including vasoconstrictor assays, are used to compare and predict potencies and/or clinical efficacies of the topical corticosteroids. There is some evidence to suggest that a recognizable correlation exists between vasoconstrictor potency and therapeutic efficacy in man.

Pharmacokinetics
The extent of percutaneous absorption of topical corticosteroids is determined by many factors including the vehicle, the integrity of the epidermal barrier, and the use of occlusive dressings (see DOSAGE AND ADMINISTRATION).

Topical corticosteroids can be absorbed from normal intact skin. Inflammation and/or other disease processes in the skin increase percutaneous absorption. Occlusive dressings substantially increase the percutaneous absorption of topical corticosteroids (see DOSAGE AND ADMINISTRATION).

Once absorbed through the skin, topical corticosteroids are handled through pharmacokinetic pathways similar to systemically administered corticosteroids. Corticosteroids are bound to plasma proteins in varying degrees. Corticosteroids are metabolized primarily in the liver and are then excreted by the kidneys. Some of the topical corticosteroids and their metabolites are also excreted into the bile.
Nystatin and Triamcinolone Acetonide
During clinical studies of mild to severe manifestations of cutaneous candidiasis, patients treated with nystatin and triamcinolone acetonide showed a faster and more pronounced clearing of erythema and pruritus than patients treated with nystatin or triamcinolone acetonide alone.

INDICATIONS AND USAGE

Nystatin and triamcinolone acetonide cream, USP is indicated for the treatment of cutaneous candidiasis; it has been demonstrated that the nystatin-steroid combination provides greater benefit than the nystatin component alone during the first few days of treatment.

CONTRAINDICATIONS

This preparations is contraindicated in those patients with a history of hypersensitivity to any of their components.

PRECAUTIONS

General

Systemic absorption of topical corticosteroids has produced reversible hypothalamic-pituitary-adrenal (HPA) axis suppression, manifestations of Cushing's syndrome, hyperglycemia, and glucosuria in some patients. Conditions that augment systemic absorption include application of the more potent steroids, use over large surface areas, prolonged use, and the addition of occlusive dressings (see DOSAGE AND ADMINISTRATION).
Therefore, patients receiving a large dose of any potent topical steroid applied to a large surface area should be evaluated periodically for evidence of HPA axis suppression by using the urinary free cortisol and ACTH stimulation tests, and for impairment of thermal homeostasis. If HPA axis suppression or elevation of the body temperature occurs, an attempt should be made to withdraw the drug, to reduce the frequency of application, or substitute a less potent steroid.
Recovery of HPA axis function and thermal homeostasis are generally prompt and complete upon discontinuation of the drug. Infrequently, signs and symptoms of steroid withdrawal may occur, requiring supplemental systemic corticosteroids.
Children may absorb proportionally larger amounts of topical corticosteroids and thus be more susceptible to systemic toxicity (see PRECAUTIONS, Pediatric Use).
If irritation or hypersensitivity develops with the combination nystatin and triamcinolone acetonide, treatment should be discontinued and appropriate therapy instituted.

Information for the Patient

Patients using this medication should receive the following information and instructions:
1. This medication is to be used as directed by the physician. It is for dermatological use only. Avoid contact with the eyes.
2. Patients should be advised not to use this medication for any disorder other than for which it was prescribed.
3. The treated skin area should not be bandaged or otherwise covered or wrapped as to be occluded (see DOSAGE AND ADMINISTRATION).
4. Patients should report any signs of local adverse reactions.
5. When using this medication in the inguinal area, patients should be advised to apply the cream sparingly and to wear loosely fitting clothing.
6. Parents of pediatric patients should be advised not to use tight-fitting diapers or plastic pants on a child being treated in the diaper area, as these garments may constitute occlusive dressings.
7. Patients should be advised on preventive measures to avoid reinfection.

Laboratory Tests

If there is a lack of therapeutic response, appropriate microbiological studies (e.g. KOH smears and/or cultures) should be repeated to confirm the diagnosis and rule out other pathogens, before instituting another course of therapy.
A urinary free cortisol test and ACTH stimulation test may be helpful in evaluating hypothalamicpituitary- adrenal (HPA) axis suppression due to corticosteroids.

Carcinogenesis , Mutagenesis, and Impairment of Fertility

Long-term animal studies have not been performed to evaluate carcinogenic or mutagenic potential, or possible impairment of fertility in males or females.

Pregnancy:

There are no teratogenic studies with combined nystatin and triamcinolone acetonide. Corticosteroids are generally teratogenic in laboratory animals when administered systemically at relatively low dosage levels. The more potent corticosteroids have been shown to be teratogenic after dermal application in laboratory animals. Therefore, any topical corticosteroid preparation should be used during pregnancy only if the potential benefit justifies the potential risk to the fetus.
Topical preparations containing corticosteroids should not be used extensively on pregnant patients, in large amounts, or for prolonged periods of time.

Nursing Mothers

It is not known whether any component of this preparation is excreted in human milk. Because many drugs are excreted in human milk, caution should be exercised during the use of this preparation by a nursing woman.

Pediatric Use

In clinical studies of a limited number of pediatric patients ranging from two months through 12 years, nystatin and triamcinolone acetonide cream cleared or significantly ameliorated the disease state in most patients.
Pediatric patients may demonstrate greater susceptibility to topical corticosteroid-induced hypothalamic-pituitary-adrenal (HPA) axis suppression and Cushing's syndrome than mature patients because of a larger skin surface area to body weight ratio.
HPA axis suppression, Cushing's syndrome, and intracranial hypertension have been reported in children receiving topical corticosteroids. Manifestations of adrenal suppression in children include linear growth retardation, delayed weight gain, low plasma cortisol levels, and absence of response to ACTH stimulation. Manifestations of intracranial hypertension include bulging fontanelles, headaches, and bilateral papilledema.
Administration of topical corticosteroids to children should be limited to the least amount compatible with an effective therapeutic regimen. Chronic corticosteroid therapy may interfere with the growth and development of children.

ADVERSE REACTIONS

A single case (approximately one percent of patients studied) of acneiform eruption occurred with use of combined nystatin and triamcinolone acetonide in clinical studies.
Nystatin is virtually nontoxic and nonsensitizing and is well tolerated by all age groups, even during prolonged use. Rarely, irritation may occur.
The following local adverse reactions are reported infrequently with topical corticosteroids (reactions are listed in an approximate decreasing order of occurrence): burning, itching, irritation, dryness, folliculitis, hypertrichosis, acneiform eruptions, hypopigmentation, perioral dermatitis, allergic contact dermatitis, maceration of the skin, perioral secondary infection, skin atrophy, striae and miliaria.

OVERDOSAGE

Topically applied corticosteroids can be absorbed in sufficient amounts to produce systemic effects (see PRECAUTIONS, General); however, acute overdosage and serious adverse effects with dermatologic use are unlikely.

DOSAGE AND ADMINISTRATION

Nystatin and triamcinolone acetonide cream is usually applied to the affected areas twice daily in the morning and evening by gently and thoroughly massaging the preparation into the skin. The cream should be discontinued if symptoms persist after 25 days of therapy (see PRECAUTIONS, Laboratory Tests).
Nystatin and triamcinolone acetonide cream should not be used with occlusive dressings.

HOW SUPPLIED

Nystatin and triamcinolone acetonide cream USP supplied in 15 gram, 30 gram and 60 gram tubes.
30 gram Tube NDC 68788-8662-3 (1 tube per carton)
STORAGE
Store at 20° to 25°C (68° to 77°F); excursions permitted between 15° to 30°C (59° to 86°F) [See USP Controlled Room Temperature]. Avoid freezing.
Manufactured for:
Macleods Pharma USA, Inc.
Princeton, NJ 08540

Manufacturer by:
Macleods Pharmaceuticals Limited
At Oxalis Labs
Baddi, Himachal Pradesh, INDIA

Rev. 09/2023

Relabeled By: Preferred Pharmaceuticals Inc.

PACKAGE LABEL.PRINCIPAL DISPLAY PANEL

Nystatin and Triamcinolone Acetonide Cream USP, 100,000 units/gram and 1 mg/gram
Pack Count: 30 gm Tube
NDC: 68788-8662-3